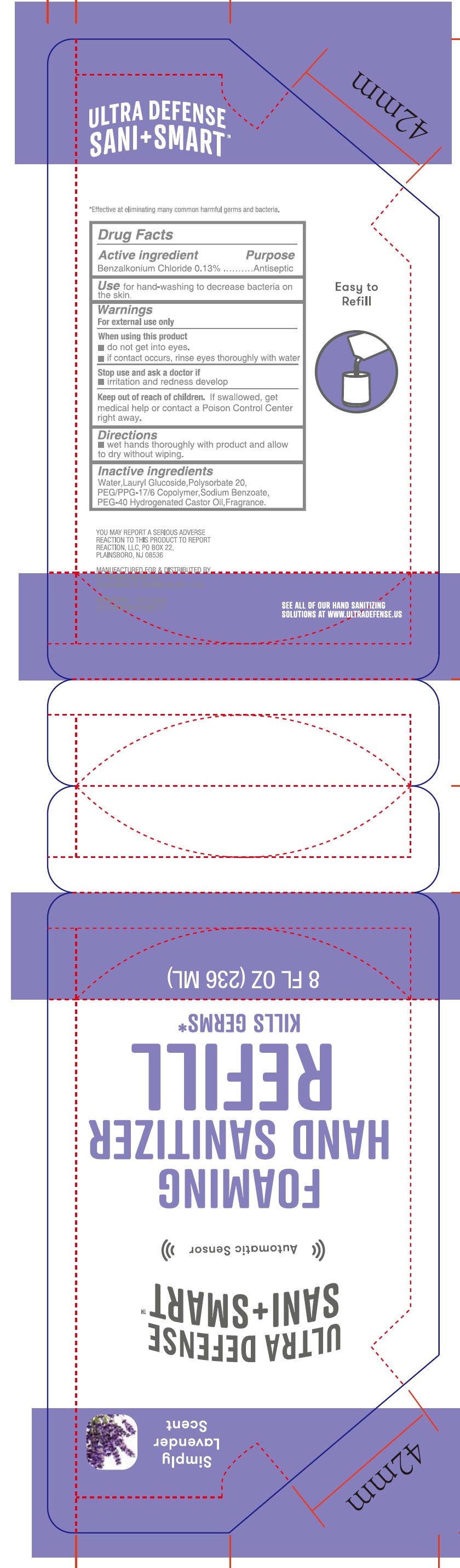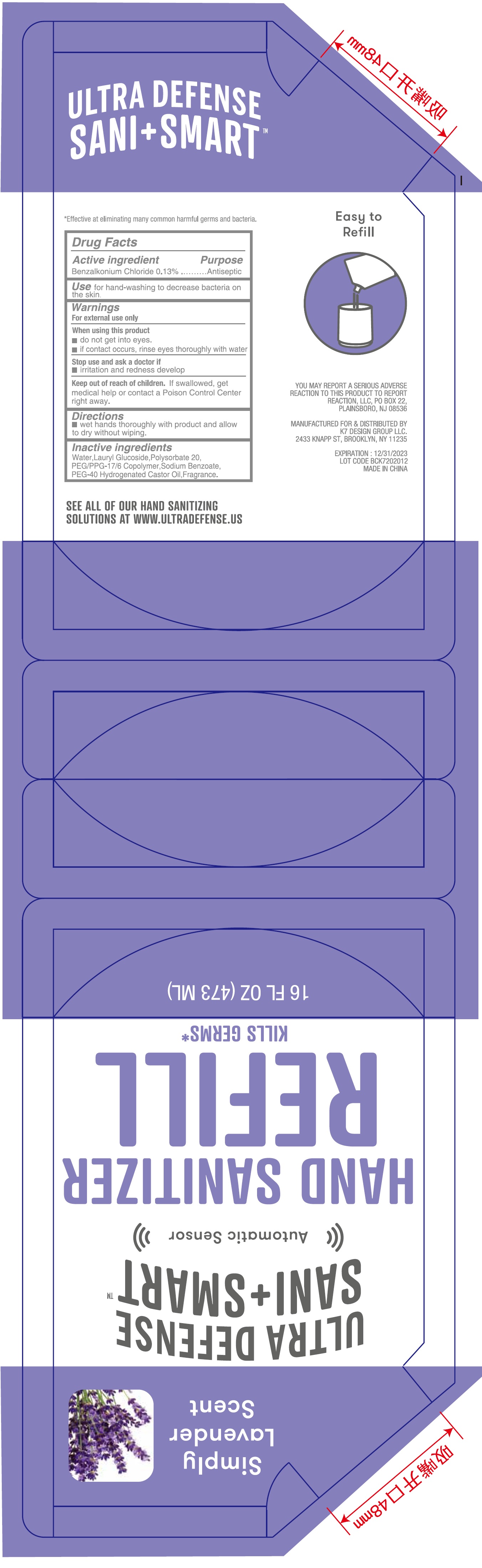 DRUG LABEL: Simply Lavender Scent FOAMING HAND SANITIZER
NDC: 74177-042 | Form: LIQUID
Manufacturer: K7 DESIGN GROUP INC
Category: otc | Type: HUMAN OTC DRUG LABEL
Date: 20231026

ACTIVE INGREDIENTS: BENZALKONIUM CHLORIDE 1.3 mg/1 mL
INACTIVE INGREDIENTS: WATER; LAURYL GLUCOSIDE; POLYSORBATE 20; PEG/PPG-17/6 COPOLYMER; SODIUM BENZOATE; POLYOXYL 40 HYDROGENATED CASTOR OIL

Simply Lavender Scent FOAMING HAND SANITIZER

Active ingredient

Benzalkonium Chloride 0.13%

Purpose

Antiseptic

Use

for hand-washing to decrease bacteria on the skin.

Warnings

For external use only

When using this product

- do not get into eyes.
- if contact occurs, rinse eyes thoroughly with water

Stop use and ask a doctor if

- irritation and redness develop

Keep out of reach of children.

If swallowed, get medical help or contact a Poison Control Center right away

Directions

- wet hands thoroughly with product and allow to dry without wiping.

Inactive ingredients

Water, Lauryl Glucoside, Polysorbate 20, PEG/PPG-17/6 Copolymer, Sodium Benzoate, PEG-40 Hydrogenated Caster Oil, Fragrance.